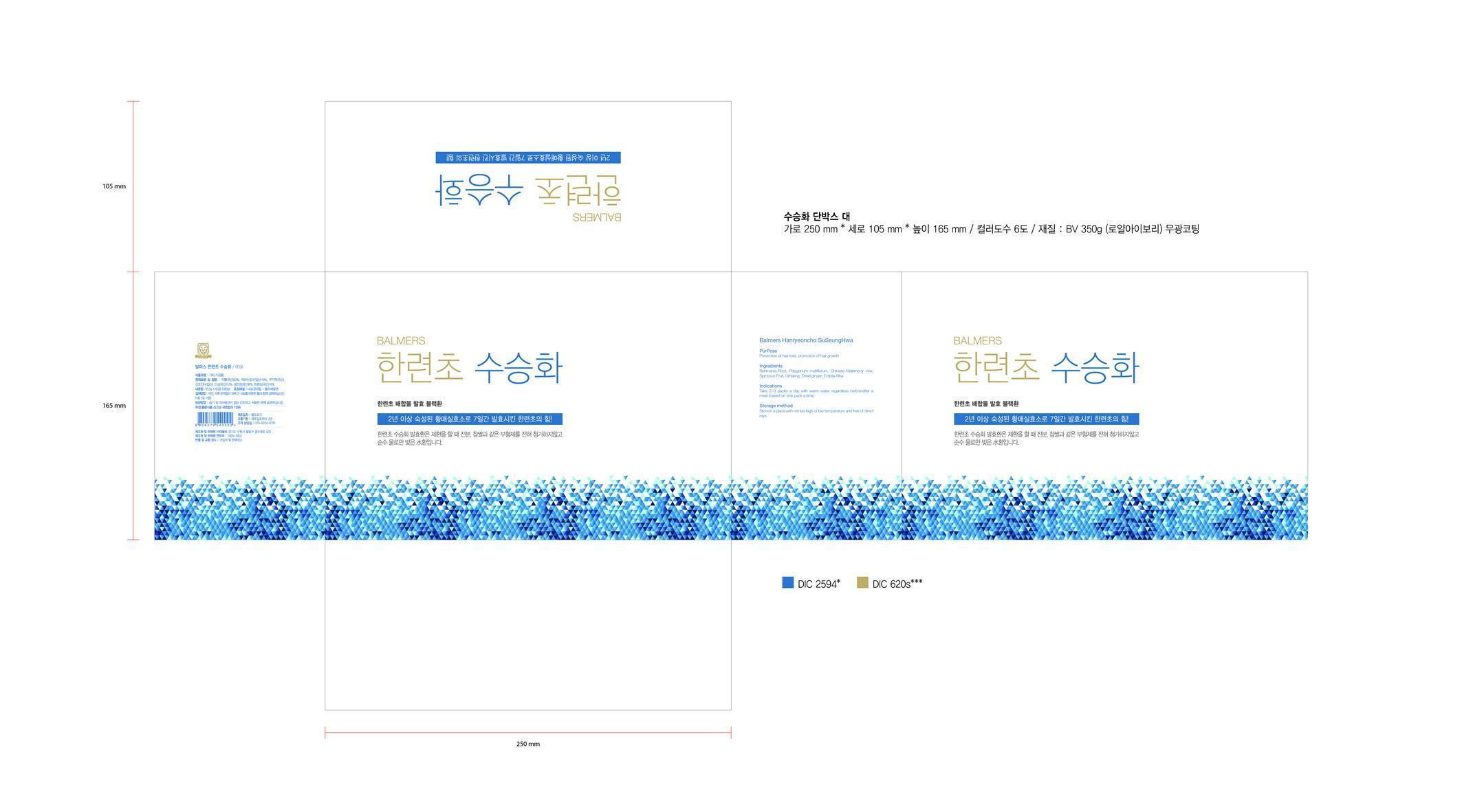 DRUG LABEL: Balmers Hanryeoncho SuSeungHwa
NDC: 69927-004 | Form: PILL
Manufacturer: Tae Eul Bi Co., Ltd.
Category: otc | Type: HUMAN OTC DRUG LABEL
Date: 20150720

ACTIVE INGREDIENTS: FALLOPIA MULTIFLORA ROOT 18 g/100 g
INACTIVE INGREDIENTS: WATER; SODIUM CHLORIDE

Drug Facts

ACTIVE INGREDIENT

polygonum multiflorum

INACTIVE INGREDIENT

rehmania, chinese matrimony vine, spinosus fruit, ginseng, dried ginger, eclipta alba

PURPOSE

hair grower and hair loss prevention

keep out of reach of the children

INDICATIONS AND USAGE

Take 2~3 packs a day with warm water regardless before/after a meal (based on one pack a time)

WARNINGS

store in a place with not to high or low temperature and free of direct rays

DOSAGE AND ADMINISTRATION

for external use only